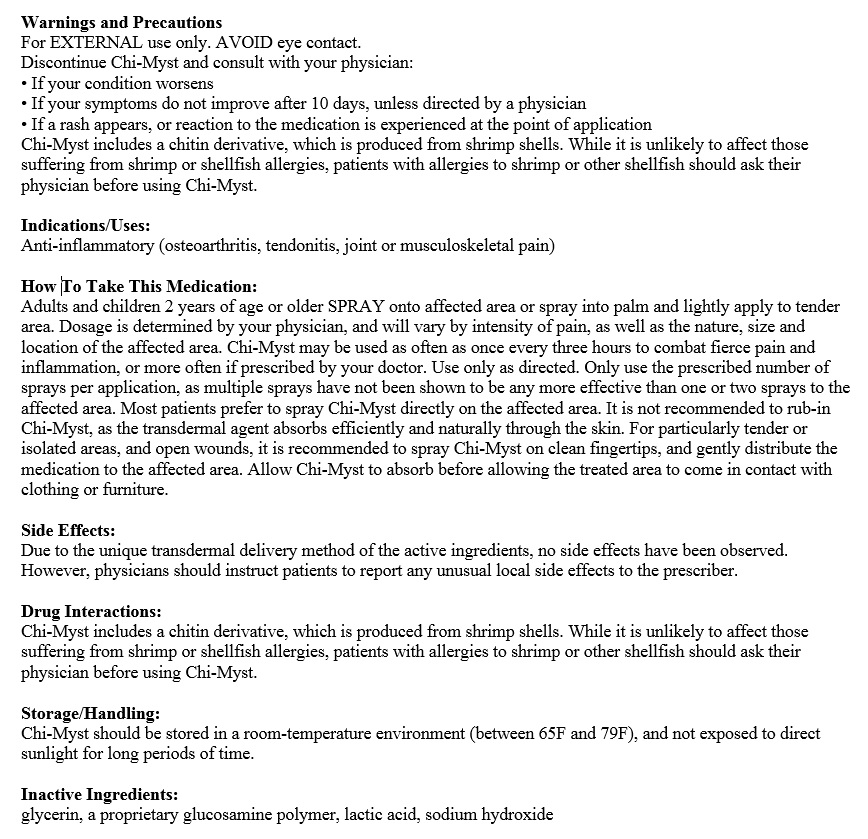 DRUG LABEL: Chi-Myst Synergy
NDC: 70486-100 | Form: SPRAY, METERED
Manufacturer: Prescription Care LLC
Category: prescription | Type: HUMAN PRESCRIPTION DRUG LABEL
Date: 20170113

ACTIVE INGREDIENTS: BUPIVACAINE HYDROCHLORIDE 0.3 g/100 mL; KETOROLAC TROMETHAMINE 1.5 g/100 mL; CHITOSAN LOW MOLECULAR WEIGHT (20-200 MPA.S) 0.1 g/100 mL; LIDOCAINE HYDROCHLORIDE 5 g/100 mL
INACTIVE INGREDIENTS: GLYCERIN 1 mL/100 mL; WATER 100 mL/100 mL; LACTIC ACID LACTATE, DL- 0.14 mL/100 mL; SODIUM HYDROXIDE 0.065 g/100 mL

Chi-Myst Synergy Topical